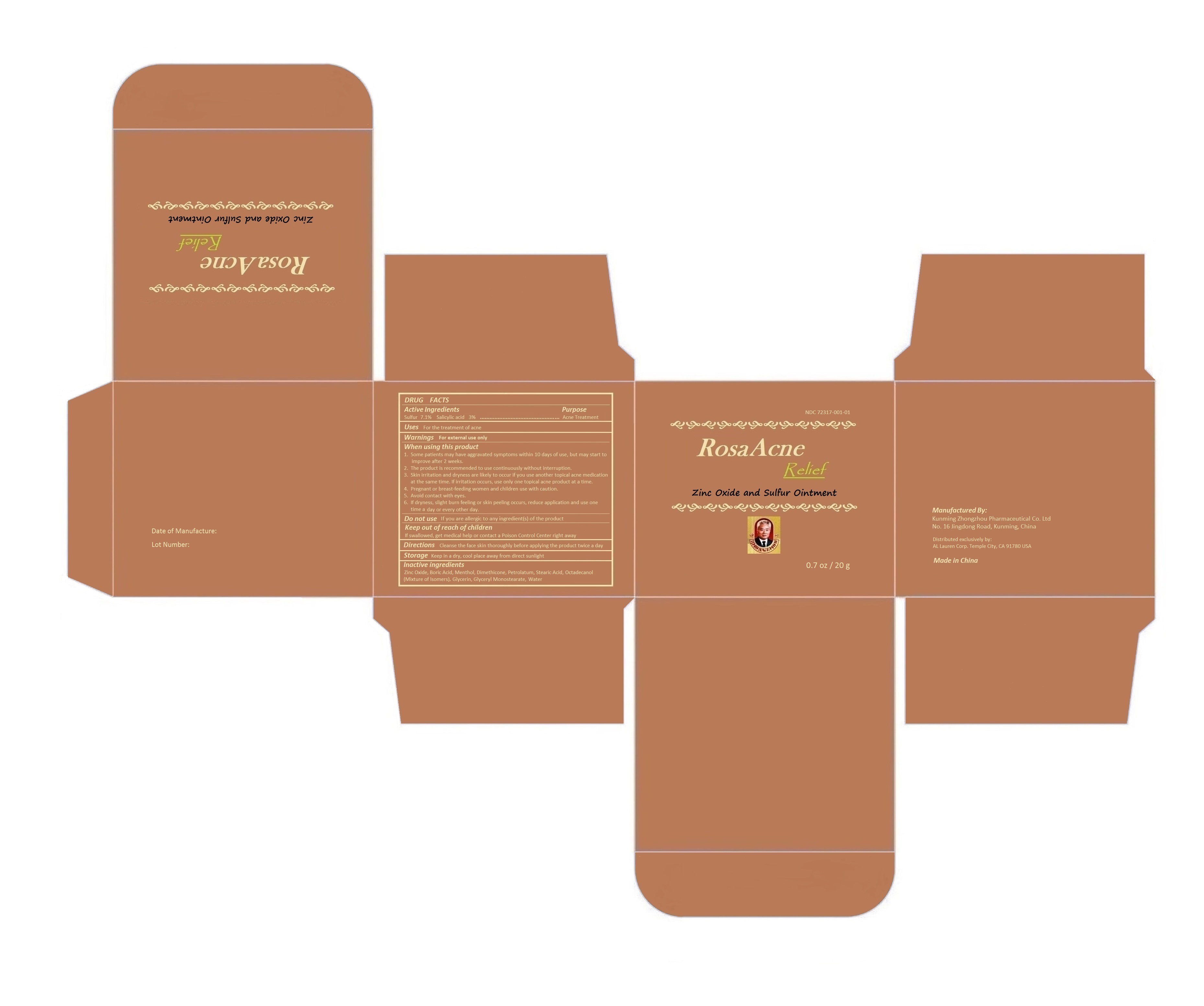 DRUG LABEL: RosaAcne Relief
NDC: 72317-001 | Form: OINTMENT
Manufacturer: Kunming Zhongzhou Pharmaceutical Co, Ltd
Category: otc | Type: HUMAN OTC DRUG LABEL
Date: 20180730

ACTIVE INGREDIENTS: SULFUR 7.1 g/100 g; SALICYLIC ACID 3 g/100 g
INACTIVE INGREDIENTS: Zinc Oxide; Boric Acid; Menthol; Dimethicone; Petrolatum; Stearic Acid; OCTADECANOL (MIXTURE OF ISOMERS); Glycerin; Glyceryl Monostearate; WATER

Kunming Zhongzhou Pharmaceutical Co, Ltd

Active Ingredients

Sulfur 7.1%
Salicylic Acid 3%

Purpose

Acne Treatment

Uses

For the treatment of acne

Warning

For external use only.

When using this product

1. Some patients may have aggravated symptoms within 10 days of use; but may start to improve after 2 weeks.
2. The product is recommended to use continuously without interruption.
3. Skin irritation and dryness are likely to occur if you use another topical acne medication at the same time. If irritation occurs, use only one topical acne product at a time.
4. Pregnant or breast-feeding women and children use with caution.
5. Avoid contact with eyes.
6. If dryness, slight burn feeling or skin peeling occurs, reduce application and use one time a day or every other day.

Do not use

If you are allergic to any ingredient(s) of the product.

Keep out of reach of children.

If swallowed, get medical help or contact a Poison Control Center right away.

Directions

Cleanse the skin thoroughly before applying this product twice a day.

Storage

Keep in a dry, cool place away from direct sunlight.

Manufactured by: Kunming Zhongzhou Pharmaceutical Co. Ltd No. 16 Jingdong Road, Kunming, China Made in China

Distributed exclusively by:
AL Lauren Corp. Temple City, CA 91780 USA

Inactive Ingredients

Zinc Oxide, Boric Acid, Menthol, Dimethicone, Petrolatum, Stearic Acid, Octadecanol (Mixture of Isomers), Glycerin,
Glyceryl Monostearate, Water